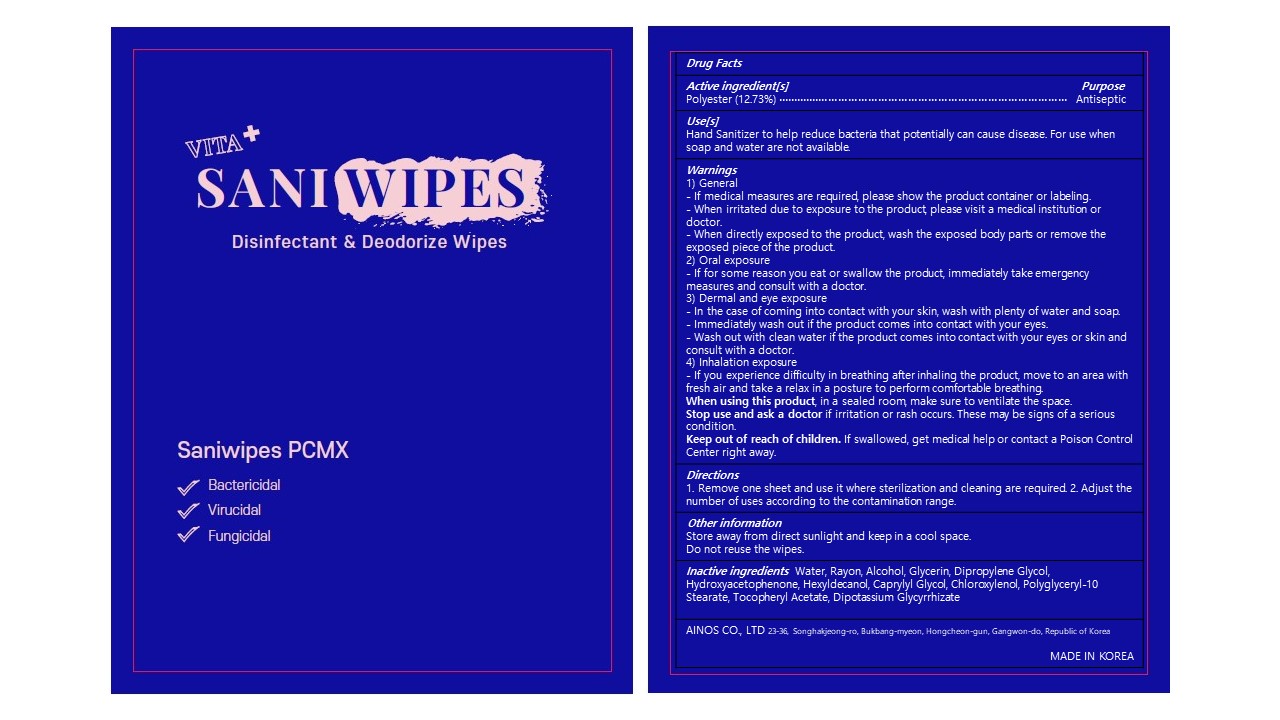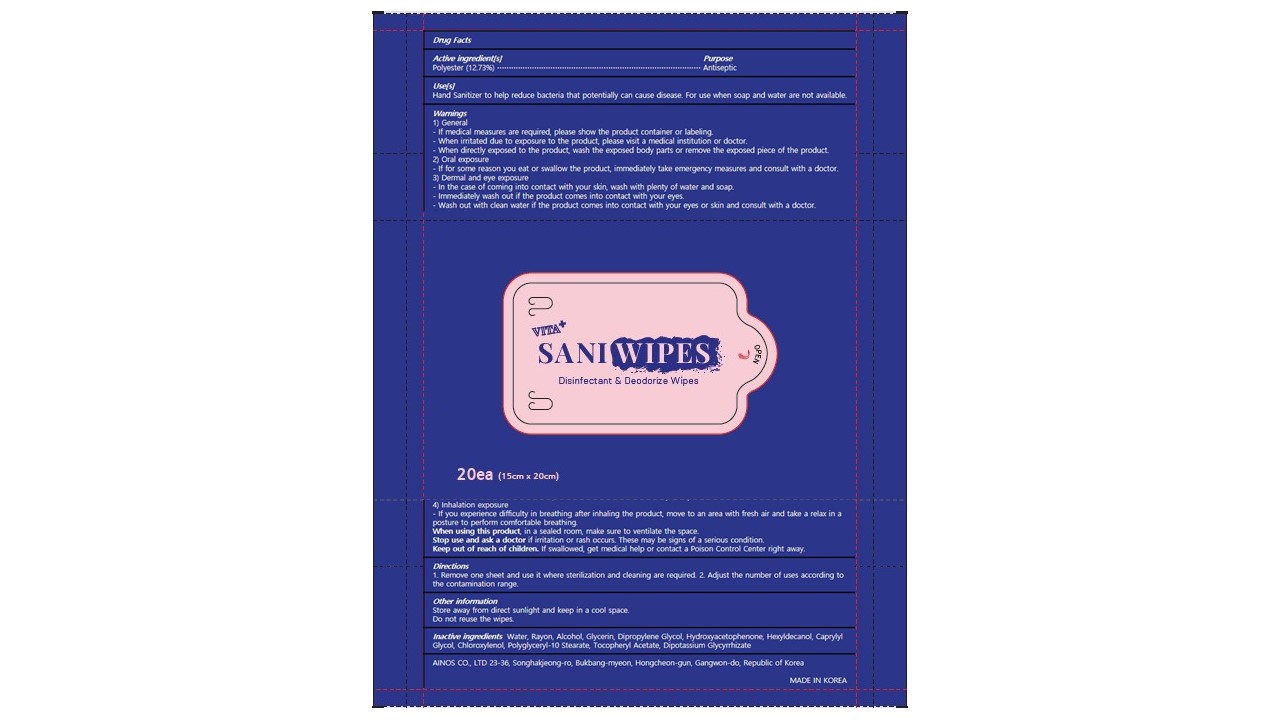 DRUG LABEL: VITA PLUS SANIWIPES
NDC: 81456-201 | Form: LIQUID
Manufacturer: AINOS CO., LTD
Category: otc | Type: HUMAN OTC DRUG LABEL
Date: 20210210

ACTIVE INGREDIENTS: CHLOROXYLENOL 0.2 g/100 g; ALCOHOL 3.97 g/100 g
INACTIVE INGREDIENTS: WATER; REGENERATED CELLULOSE; HEXYLDECANOL; POLYESTER (ADIPIC ACID, 1,6-HEXANEDIOL, NEOPENTYL GLYCOL); GLYCERIN; DIPROPYLENE GLYCOL; .ALPHA.-TOCOPHEROL ACETATE; POLYGLYCERYL-10 STEARATE; GLYCYRRHIZINATE DIPOTASSIUM; HYDROXYACETOPHENONE; CAPRYLYL GLYCOL

Active Ingredient

Alcohol 3.97%

Chloroxylenol 0.2%

Purpose

Antiseptic

Use[s]

Hand Sanitizer to help reduce bacteria that potentially can cause disease. For use when soap and water are not available.

Warnings

1) General

- If medical measures are required, please show the product container or labeling.

- When irritated due to exposure to the product, please visit a medical institution or doctor.

- When directly exposed to the product, wash the exposed body parts or remove the exposed piece of the product.

2) Oral exposure

- If for some reason you eat or swallow the product, immediately take emergency measures and consult with a doctor.

3) Dermal and eye exposure

- In the case of coming into contact with your skin, wash with plenty of water and soap.

- Immediately wash out if the product comes into contact with your eyes.

- Wash out with clean water if the product comes into contact with your eyes or skin and consult with a doctor.

4) Inhalation exposure

- If you experience difficulty in breathing after inhaling the product, move to an area with fresh air and take a relax in a posture to perform comfortable breathing.

When using this product

in a sealed room, make sure to ventilate the space.

Stop use and ask a doctor

if irritation or rash occurs. These may be signs of a serious condition.

Keep out of reach of children.

If swallowed, get medical help or contact a Poison Control Center right away.

Directions

1. Remove one sheet and use it where sterilization and cleaning are required. 2. Adjust the number of uses according to the contamination range.

Other information

Store away from direct sunlight and keep in a cool space.

Do not reuse the wipes.

Inactive ingredients

Water, Rayon, Polyester, Glycerin, Dipropylene Glycol, Hydroxyacetophenone, Hexyldecanol, Caprylyl Glycol, Polyglyceryl-10 Stearate, Tocopheryl Acetate, Dipotassium Glycyrrhizate